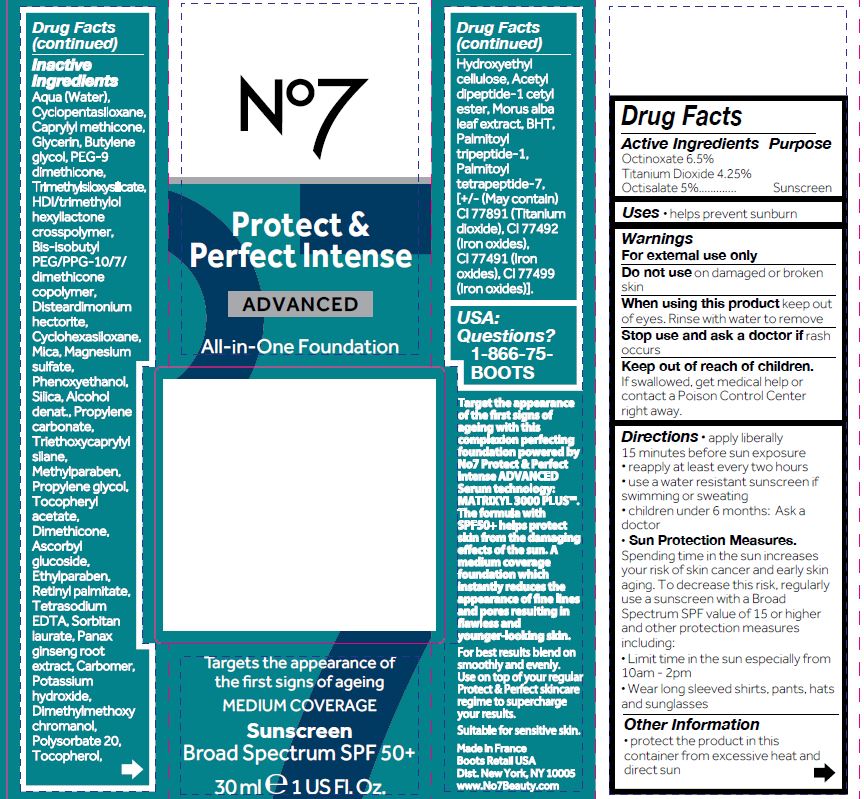 DRUG LABEL: No7 Perfect and Perfect Intense Advanced All in One Foundation SPF 50 Amber
NDC: 61589-0216 | Form: CREAM
Manufacturer: BCM Cosmetique SAS
Category: otc | Type: HUMAN OTC DRUG LABEL
Date: 20241016

ACTIVE INGREDIENTS: Octinoxate 1.95 g/30 g; TITANIUM DIOXIDE 1.275 g/30 g; OCTISALATE 1.5 g/30 g
INACTIVE INGREDIENTS: WATER; CYCLOMETHICONE; GLYCEROL FORMAL; BUTYLENE GLYCOL; PEG-9 DIMETHICONE; GLYCERIN; TRIMETHYLSILOXYSILICATE (M/Q 0.8-1.0); HEXAMETHYLENE DIISOCYANATE/TRIMETHYLOL HEXYLLACTONE CROSSPOLYMER; DIMETHICONE/BIS-ISOBUTYL PPG-20 CROSSPOLYMER; DISTEARDIMONIUM HECTORITE; MICA; MAGNESIUM SULFATE, UNSPECIFIED; PHENOXYETHANOL; SILICON DIOXIDE; ALCOHOL; PROPYLENE CARBONATE; TRIETHOXYCAPRYLYLSILANE; METHYLPARABEN; PROPYLENE GLYCOL; PEG/PPG-14/7 DIMETHYL ETHER; .ALPHA.-TOCOPHEROL ACETATE; DIMETHICONE; ASCORBYL GLUCOSIDE; ETHYLPARABEN; VITAMIN A PALMITATE; EDETATE SODIUM; SORBITAN MONOLAURATE; CARBOMER 940; PANAX GINSENG ROOT OIL; POTASSIUM HYDROXIDE; DIMETHYLMETHOXY CHROMANOL; POLYSORBATE 20; TOCOPHEROL; HYDROXYETHYL CELLULOSE, UNSPECIFIED; N-ACETYL DIPEPTIDE-1; BUTYLATED HYDROXYTOLUENE; MORUS ALBA LEAF; .ALPHA.-TOCOPHEROL, DL-; BROWN IRON OXIDE; FERRIC OXIDE RED; FERROSOFERRIC OXIDE

No7 Protect and Perfect Intense Advanced All in One Foundation SPF 50 Amber

Carton Active Ingredients Section

Active Ingredients

Octinoxate 6.5%

Titanium dioxide 4.25%

Octisalate 5%

Purpose

Sunscreen

Uses

Uses - helps prevent sunburn

Warnings

For external use only

Do not use on damaged or broken skin

When using this product keep out of eyes. Rinse with water to remove

Warnings

For external use only

Do not use on damaged or broken skin

When using this product keep out of eyes. Rinse with water to remove

Ask a doctor

Stop use and ask a doctor if rash occurs.

Keep out of reach of children. If swallowed, get medical help or contact a Poison Control Center right away.

Directions

apply liberally 15 minutes before sun exposure

reapply at least every 2 hours

use a water resistant sunscreen if swimming or sweating

children under 6 monhts of age: Ask a doctor

Sun Protection Measures. Spending time in the sun increases your risk of skin cancer and early skin aging. To decrease this risk, regularly use a sunscreen with a Broad Spectrum SPF value of 15 or higher and other sun protection measures including:

limit time in the sun, especially from 10 a.m. - 2 p.m.

wear long-sleeved shirts, pants, hats, and sunglasses

Directions

apply liberally 15 minutes before sun exposure

reapply at least every 2 hours

use a water resistant sunscreen if swimming or sweating

children under 6 monhts of age: Ask a doctor

Sun Protection Measures. Spending time in the sun increases your risk of skin cancer and early skin aging. To decrease this risk, regularly use a sunscreen with a Broad Spectrum SPF value of 15 or higher and other sun protection measures including:

limit time in the sun, especially from 10 a.m. - 2 p.m.

wear long-sleeved shirts, pants, hats, and sunglasses

Other information

Protect the product in this container from excessive heat and direct sun

Inactive ingredients

Aqua (Water), Cyclopentasiloxane, Caprylyl methicone, Glycerin, Butylene glycol, PEG-9 dimethicone, Trimethylsiloxysilicate, HDI/trimethylol hexyllactone crosspolymer, Bis-isobutyl peg/ppg-10/7/dimethicone copolymer, Disteardimonium hectorite, Cyclohexasiloxane, Mica, Magnesium sulfate, Phenoxyethanol, Silica, Alcohol denat., Propylene carbonate, Triethoxycaprylylsilane, Methylparaben, Propylene glycol, Tocopheryl acetate, Dimethicone, Ascorbyl glucoside, Ethylparaben, Retinyl palmitate, Tetrasodium EDTA, Sorbitan laurate, Panax ginseng extract, Carbomer, Potassium hydroxide, Dimethylmethoxy chromanol, Polysorbate 20, Tocopherol, Hydroxyethyl cellulose, Acetyl dipeptide-1 cetyl ester, Morus alba extract, BHT, Palmitoyl Tripeptide-1, Palmitoyl tetrapeptide-7 [+/- (May Contain) CI 77891 (Titanium Dioxide), CI 77492 (Iron oxides), CI 77491 (Iron oxides), CI 77499 (Iron oxides)].

Description

No7

Protect & Perfect Intense ADVANCED All-in-One Foundation

Targets the appearance of the first signs of ageing

MEDIUM COVERAGE

Sunscreen

Broad Spectrum SPF 50+

30 ml e 1 US Fl. Oz.

Target the appearance of the first signs of ageing with this complexion perfecting foundation powered by No7 Protect & Perfect Intense Advanced Serum technology: MATRIXYL 3000 PLUSTM.The formula with SPF50+ helps protect skin from the damaging effects of the sun. A medium coverage foundation which instantly reduces the appearance of fine lines and pores resulting in flawless and younger-looking skin.

Information

Made in France

Boots Retail USA

Distr. New York, NY 10005

www.No7Beauty.com

Carton